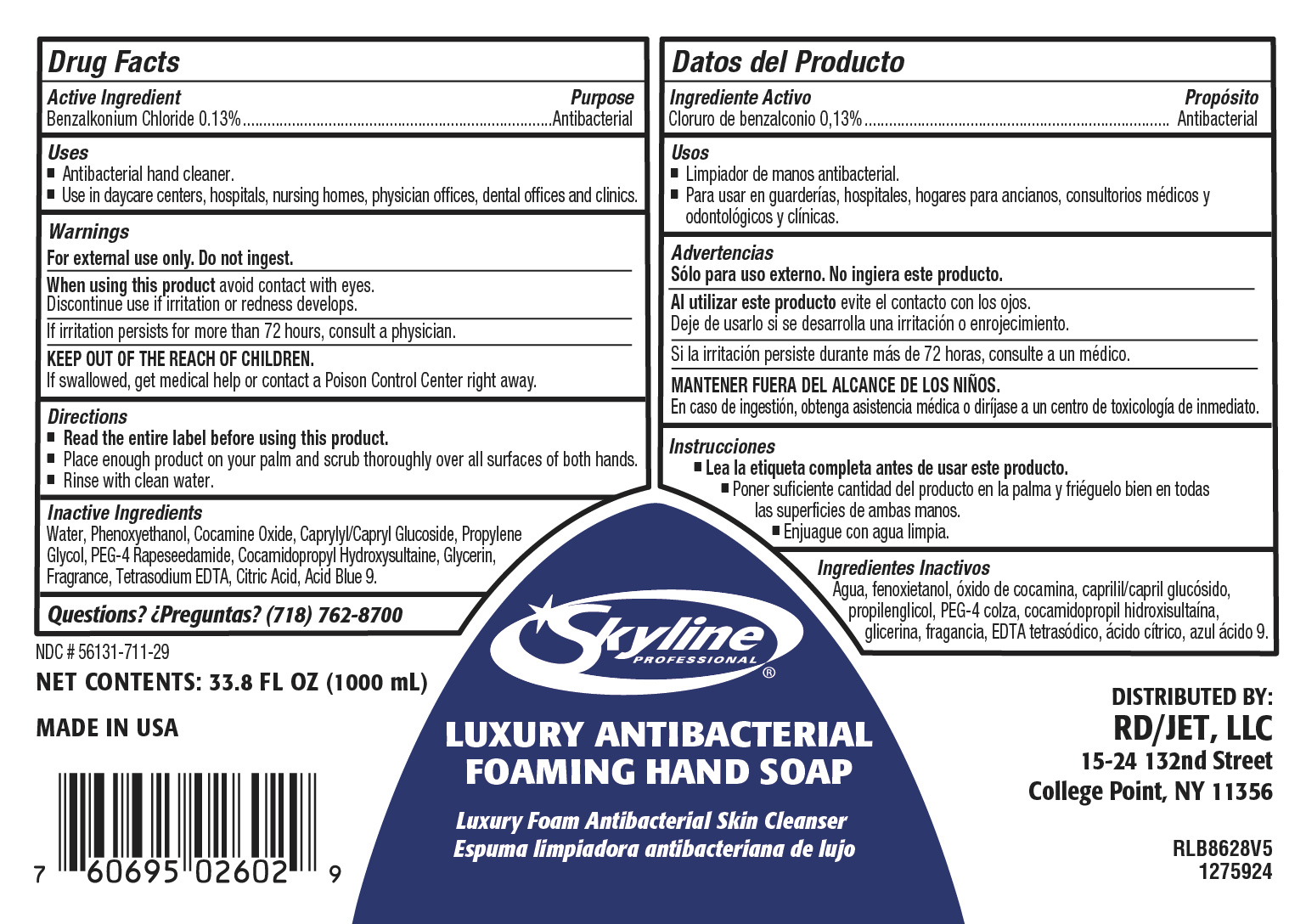 DRUG LABEL: Luxury Antibacterial Foaming HandSoap
NDC: 56131-859 | Form: LIQUID
Manufacturer: RD Food Service DBA Restaurant Depot
Category: otc | Type: HUMAN OTC DRUG LABEL
Date: 20241226

ACTIVE INGREDIENTS: BENZALKONIUM CHLORIDE 1.3 mg/100 mL
INACTIVE INGREDIENTS: N-ALKYL DIMETHYL BENZYL AMMONIUM CHLORIDE (C12-C18); .BETA.-CITRONELLOL, (+/-)-; GLYCERIN; COCAMINE OXIDE; SODIUM CHLORIDE; LIME OIL; COCAMIDOPROPYL HYDROXYSULTAINE; SODIUM HYDROXIDE; CITRAL; PHENOXYETHANOL; SODIUM GLYCOLATE; EDETATE SODIUM; ALCOHOL; FD&C BLUE NO. 1; LINALOOL; TRISODIUM NITRILOTRIACETATE; ANHYDROUS CITRIC ACID; METHYL DIHYDROJASMONATE (SYNTHETIC); METHYLCHLOROISOTHIAZOLINONE; PEG-4 RAPESEEDAMIDE; PROPYLENE GLYCOL; 2,4-DIMETHYL-3-CYCLOHEXENE CARBOXALDEHYDE; CAPRYLYL/CAPRYL GLUCOSIDE; MAGNESIUM NITRATE; 2-METHYLUNDECANAL; METHYLISOTHIAZOLINONE; BENZYL ACETATE; GERANIOL; ALLYL CYCLOHEXANEPROPIONATE; GERANYL ACETATE; CITRONELLYL ACETATE; WATER

RD Luxury Antibacterial Foaming Hand Soap

DOSAGE AND ADMINISTRATION

Place enough product on your palm and scrub hands thoroughly over both surfaces of both hands. Rinse with clean water

INACTIVE INGREDIENT

Water, Phenoxyethanol, cocamine oxide, caprylyl/capryl glucoside, Porpylene glycol, PEG-4 rapeseedamide,cocamidopropyl hydroxysultaine, glycerin, fragrance, tetrasodium EDTA, Citric Acid, Acid Blue 9

INDICATIONS AND USAGE

Antibacterial Hand Cleaner

Use in daycare centers, hospitals, nursing homes, physicians offices, dental offices and clinics

INSTRUCTIONS FOR USE

Read entire label before using this product

place enough product on your palm and scrub thoroughly over all surfaces of both hands. Rinse with clean water.

ACTIVE INGREDIENT

Benzalkonium chloride

KEEP OUT OF REACH OF CHILDREN

If swallowed, get medical help or contact Poison Control Center right away.

PURPOSE

Antibacterial

WARNINGS

For external use only. Do not ingest

When using this product avoud contact with eyes

disocntinue use if irritation or redness develops

I irritation persist for more than 72 hours, consult a physicain